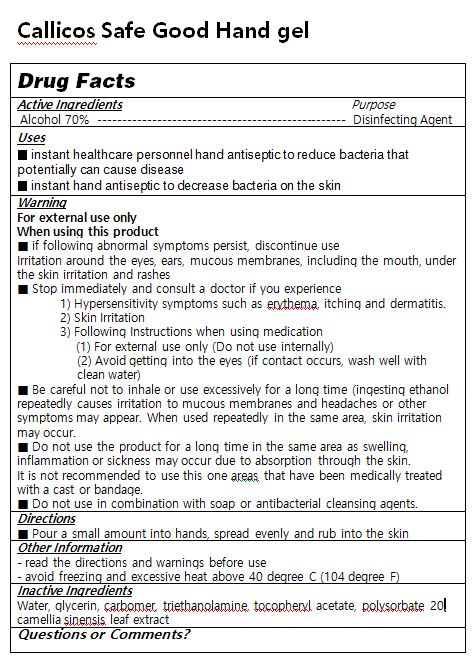 DRUG LABEL: Callicos Safe Good Hand gel
NDC: 76586-107 | Form: GEL
Manufacturer: HEALKINBIO CO.
Category: otc | Type: HUMAN OTC DRUG LABEL
Date: 20200604

ACTIVE INGREDIENTS: ALCOHOL 70 mL/100 mL
INACTIVE INGREDIENTS: WATER; TROLAMINE; GREEN TEA LEAF; POLYSORBATE 20; GLYCERIN; .ALPHA.-TOCOPHEROL ACETATE; CARBOMER 940

Active Ingredient(s)

alcohol

Purpose

Purpose: Antiseptic

Use

 Hand sanitizing to help reduce bacteria on the skin

Warnings

 For external use only.
 Flammable, keep away from fire or flame.
 When using this product, avoid contact with the eyes. In case of contact, rinse eyes thoroughly with water.
 Stop use and ask a doctor if irritation or redness appears and lasts.

 Keep out of reach of children. If swallowed, get medical help or contact a Poison Control Center immediately.

Directions

 Take suitable amount of sanitizer in the hand. Wet thoroughly and rub hands together until dry

INACTIVE INGREDIENT

water glycerin carbome triethanolamine, tocopheryl acetate, Polysorbate 20, camellia sinensis leaf extract